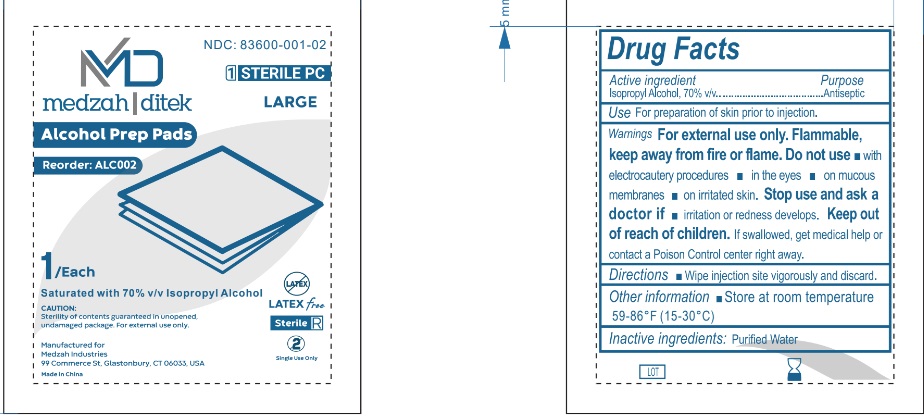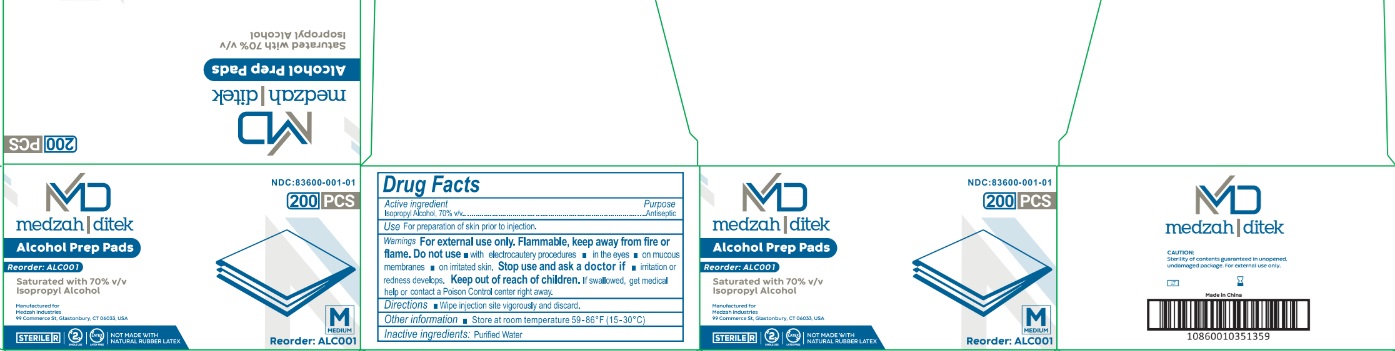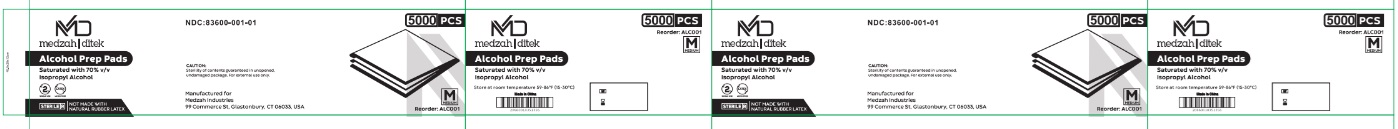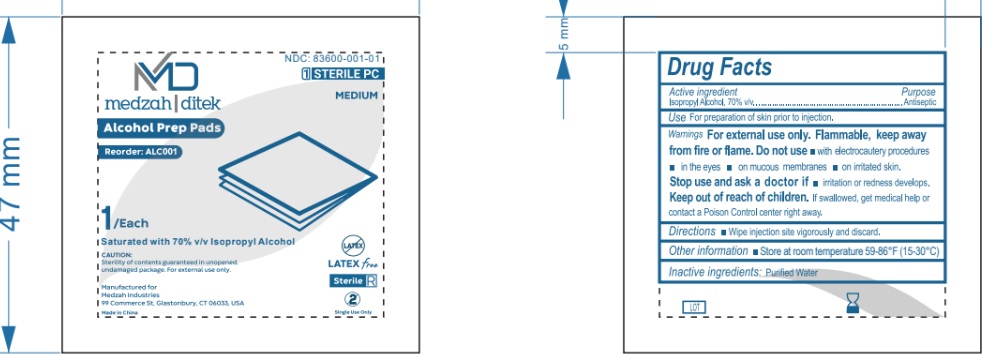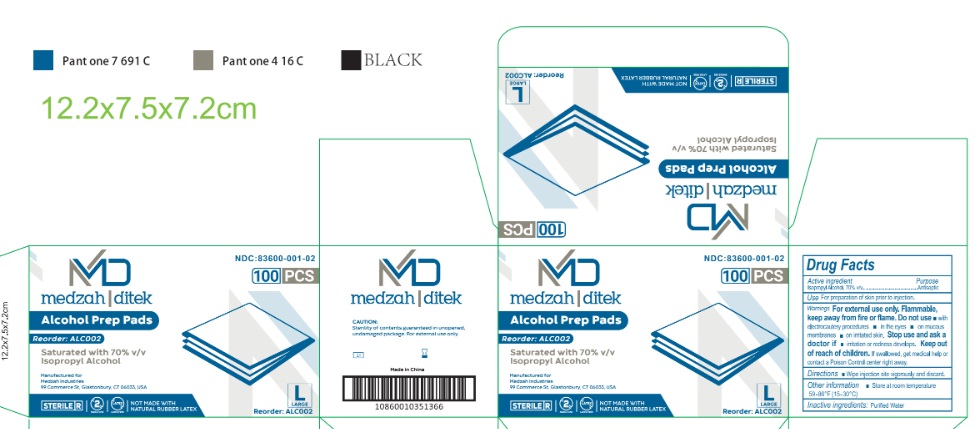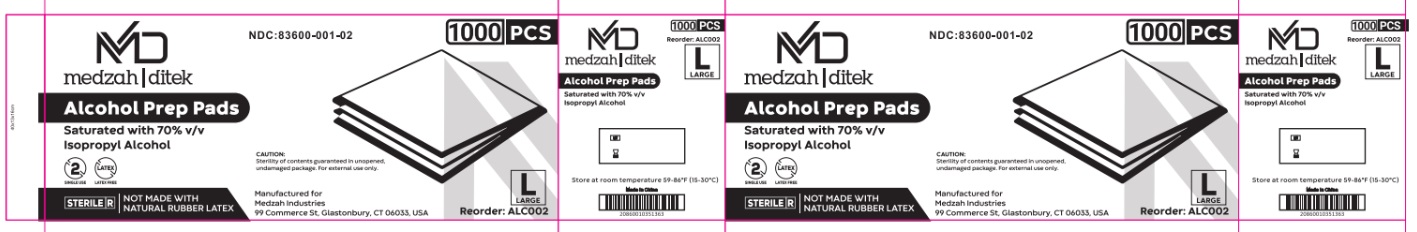 DRUG LABEL: Medzah Ditek Alcohol Prep Pads
NDC: 83600-001 | Form: CLOTH
Manufacturer: Medzah Industries
Category: otc | Type: HUMAN OTC DRUG LABEL
Date: 20250110

ACTIVE INGREDIENTS: ISOPROPYL ALCOHOL 70 mL/100 mL
INACTIVE INGREDIENTS: WATER

Active Ingredient (s)

Isopropyl Alcohol 70% V/V

Purpose

Antiseptic

Uses

For preparation of skin prior to injection.

Warnings

For external use only. Flammable, Keep away from fire or flame.

Do not use

- with a electrocautery procedures
- in the eyes
- on mucous membranes
- on irritated skin.
- Stop use and ask a doctor if- irritation or redness develops.
- Keep out of reach of children. if swallowed, get medical help or contact a Poison Control center right away.

Directions

Wipe injection site vigorously and discard.

Other information

Store at room temperature 15-30°C (59-86°F)

Inactive Ingredients

Purified Water